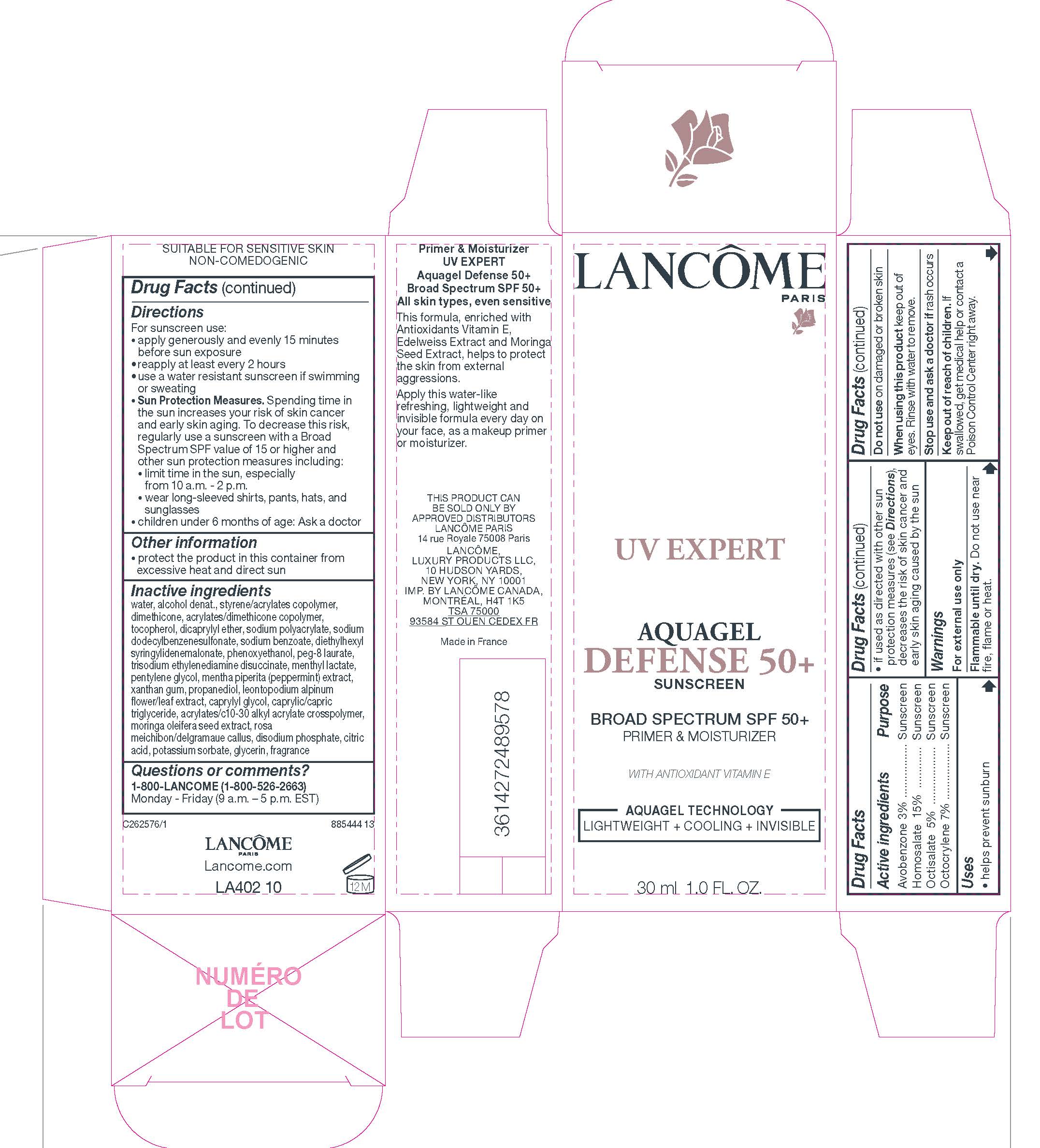 DRUG LABEL: Lancome Paris UV Expert Aquagel Defense 50 Plus Sunscreen Broad Spectrum SPF 50 Plus Primer and Moisturizer
NDC: 49967-142 | Form: CREAM
Manufacturer: L'Oreal USA Products Inc
Category: otc | Type: HUMAN OTC DRUG LABEL
Date: 20250318

ACTIVE INGREDIENTS: AVOBENZONE 30 mg/1 mL; homosalate 150 mg/1 mL; OCTISALATE 50 mg/1 mL; OCTOCRYLENE 70 mg/1 mL
INACTIVE INGREDIENTS: WATER; ALCOHOL; STYRENE/ACRYLAMIDE COPOLYMER (500000 MW); DIMETHICONE; 2-ETHYLHEXYL ACRYLATE, METHACRYLATE, METHYL METHACRYLATE, OR BUTYL METHACRYLATE/HYDROXYPROPYL DIMETHICONE COPOLYMER (30000-300000 MW); TOCOPHEROL; DICAPRYLYL ETHER; SODIUM POLYACRYLATE (2500000 MW); SODIUM DODECYLBENZENESULFONATE; SODIUM BENZOATE; DIETHYLHEXYL SYRINGYLIDENEMALONATE; PHENOXYETHANOL; PEG-8 LAURATE; TRISODIUM ETHYLENEDIAMINE DISUCCINATE; MENTHYL LACTATE, (-)-; PENTYLENE GLYCOL; MENTHA X PIPERITA WHOLE; XANTHAN GUM; PROPANEDIOL; LEONTOPODIUM NIVALE SUBSP. ALPINUM FLOWERING TOP; CAPRYLYL GLYCOL; MEDIUM-CHAIN TRIGLYCERIDES; CARBOMER INTERPOLYMER TYPE A (ALLYL SUCROSE CROSSLINKED); MORINGA OLEIFERA LEAF; SODIUM PHOSPHATE, DIBASIC, ANHYDROUS; CITRIC ACID MONOHYDRATE; POTASSIUM SORBATE; GLYCERIN

Drug Facts

Active ingredients

Avobenzone 3%

Homosalate 15%

Octisalate 5%

Octocrylene 7%

Purpose

Sunscreen

Uses

- helps prevent sunburn

- if used as directed with other sun protection measures (see Directions), decreases the risk of skin cancer and early skin aging caused by the sun

Warnings

For external use only

Flammable until dry.

Do not use near fire, flame, or heat.

Do not use

on damaged or broken skin

When using this product

keep out of eyes. Rinse with water to remove.

Stop use and ask a doctor if

rash occurs

Keep out of reach of children.

If swallowed, get medical help or contact a Poison Control Center right away.

Directions

For sunscreen use:

● apply generously and evenly 15 minutes before sun exposure

● reapply at least every 2 hours

● use a water resistant sunscreen if swimming or sweating

● Sun Protection Measures. Spending time in the sun increases your risk of skin cancer and early skin aging. To decrease this risk, regularly use a sunscreen with a Broad Spectrum SPF value of 15 or higher and other sun protection measures including:

● limit time in the sun, especially from 10 a.m. – 2 p.m.

● wear long-sleeved shirts, pants, hats, and sunglasses

● children under 6 months of age: Ask a doctor

Other information

protect the product in this container from excessive heat and direct sun

Inactive ingredients

water, alcohol denat., styrene/acrylates copolymer, dimethicone, acrylates/dimethicone copolymer, tocopherol, dicaprylyl ether, sodium polyacrylate, sodium dodecylbenzenesulfonate, sodium benzoate, diethylhexyl syringylidenemalonate, phenoxyethanol, PEG-8 laurate, trisodium ethylenediamine disuccinate, menthyl lactate, pentylene glycol, mentha piperita (peppermint) extract, xanthan gum, propanediol, leontopodium alpinum flower/leaf extract, caprylyl glycol, caprylic/capric triglyceride, acrylates/c10-30 alkyl acrylate crosspolymer, moringa oleifera seed extract, rosa meichibon/delgramaue callus, disodium phosphate, citric acid, potassium sorbate, glycerin, fragrance

Questions or comments?

1-800-LANCOME (1-800-526-2663) Monday - Friday (9 a.m. - 5 p.m. EST)